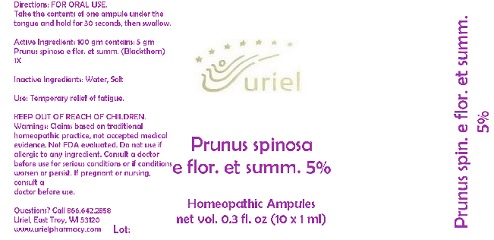 DRUG LABEL: Prunus spinosa e flor. et summ. 5
NDC: 48951-8079 | Form: LIQUID
Manufacturer: Uriel Pharmacy Inc.
Category: homeopathic | Type: HUMAN OTC DRUG LABEL
Date: 20180525

ACTIVE INGREDIENTS: SLOE 1 [hp_X]/1 mL
INACTIVE INGREDIENTS: WATER; SODIUM CHLORIDE

Prunus spinosa e flor. et summ. 5

INDICATIONS AND USAGE

Directions: FOR ORAL USE.

DOSAGE AND ADMINISTRATION

Take the contents of one ampule under the tongue and hold for 30 seconds, then swallow.

Active Ingredient: 100 gm contains: 5 gm Prunus spinosa e flor. et summ. (Blackthorn) 1X

Inactive Ingredients: Water, Salt

PURPOSE

Use: Temporary relief of fatigue.

KEEP OUT OF REACH OF CHILDREN.

WARNINGS

Warnings: Claims based on traditional homeopathic practice, not accepted medical evidence. Not FDA evaluated. Do not use if allergic to any ingredient. Consult a doctor before use for serious conditions or if conditions worsen or persist. If pregnant or nursing, consult a
doctor before use.

QUESTIONS

Questions? Call 866.642.2858 Uriel, East Troy, WI 53120 www.urielpharmacy.com